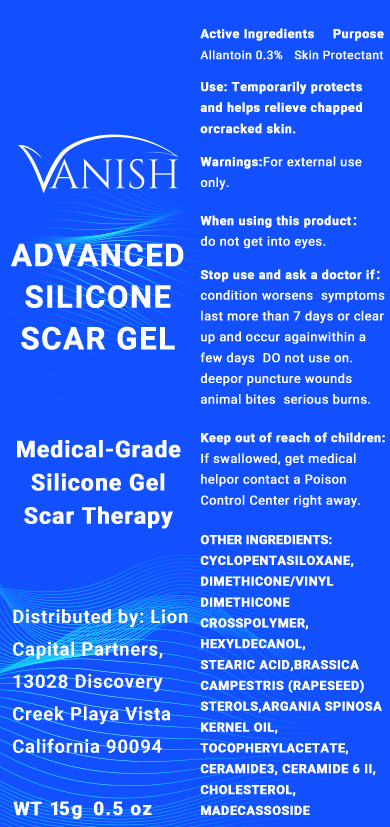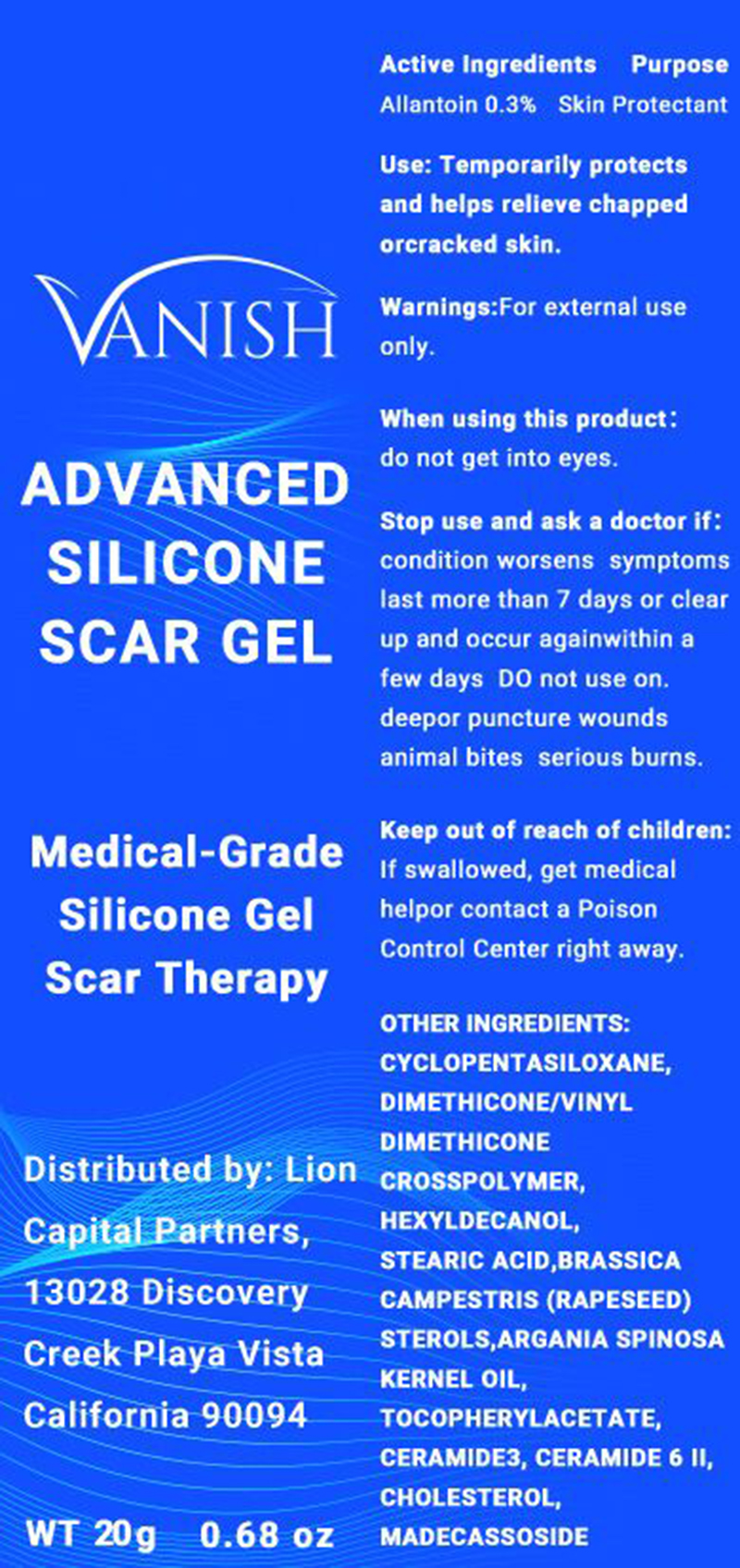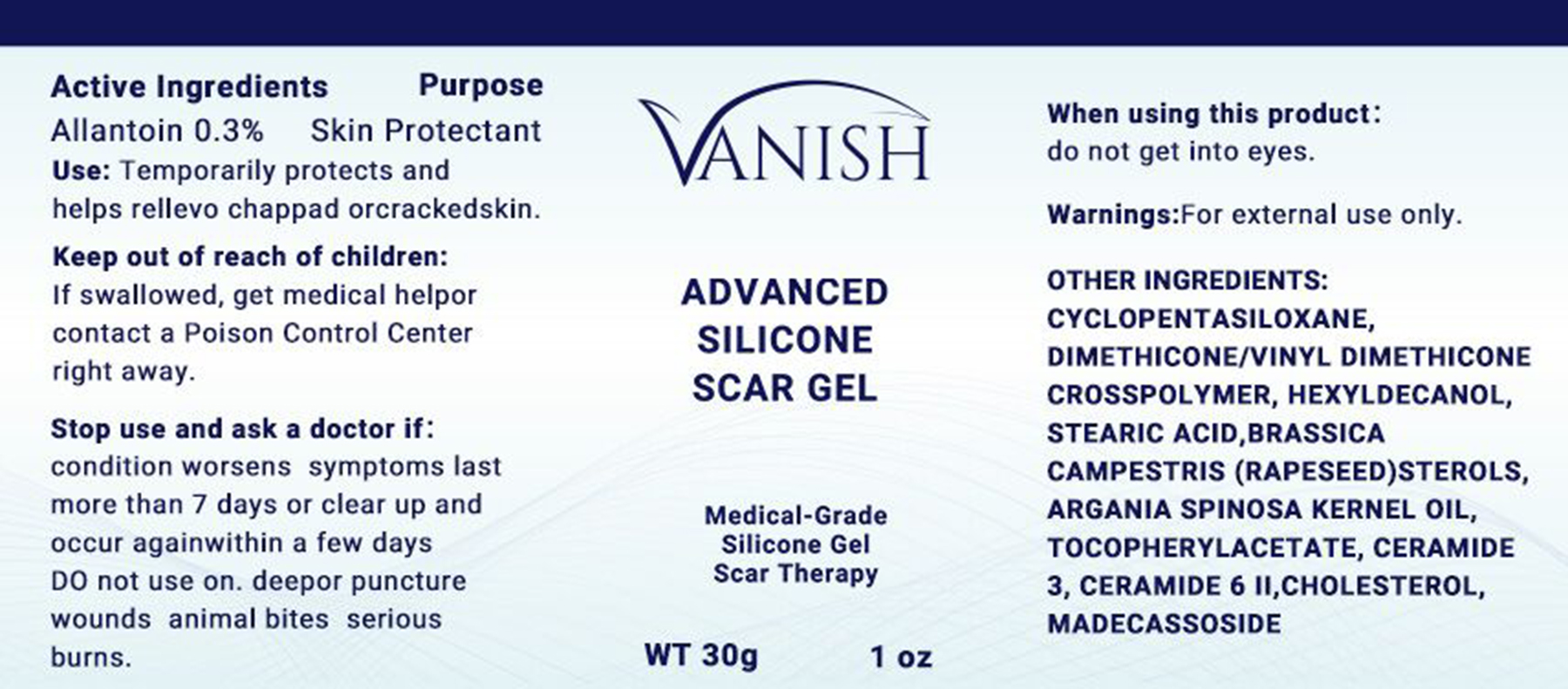 DRUG LABEL: scar gel
NDC: 75728-004 | Form: GEL
Manufacturer: Guangzhou Meayon Biotechnology Co,.Ltd
Category: otc | Type: HUMAN OTC DRUG LABEL
Date: 20220824

ACTIVE INGREDIENTS: ALLANTOIN 0.3 g/100 g
INACTIVE INGREDIENTS: HEXYLDECANOL; STEARIC ACID; RAPESEED STEROL; ARGAN OIL; .ALPHA.-TOCOPHEROL ACETATE; CERAMIDE 3; CERAMIDE 6 II; CHOLESTEROL; MADECASSOSIDE; CYCLOMETHICONE 5; DIMETHICONE/VINYL DIMETHICONE CROSSPOLYMER (SOFT PARTICLE)

75728-004
scar gel

Active Ingredient(s)

Allantoin 0.3%

Purpose

Skin Protectant

Use

Temporarily protects and helps relieve chapped or cracked skin.

Warnings

For external use only.

Do not use

/

WHEN USING

do not get into eyes.

STOP USE

condition worsens symptoms last more than 7daysor clear up and occur again within a few days DO not use on.
deep or puncture wounds animal bites serious burns.

KEEP OUT OF REACH OF CHILDREN

If swallowed, get medical help or contact a Poison Control Center right away.

Directions

condition worsens symptoms last more than 7daysor clear up and occur again within a few days DO not use on.

Other information

/

Inactive ingredients

CYCLOPENTASILOXANE
DIMETHICONE/VINYL DIMETHICONE CROSSPOLYMER

HEXYLDECANOL
STEARIC ACID
BRASSICA CAMPESTRIS (RAPESEED) STEROLS
ARGANIA SPINOSA KERNEL OIL
TOCOPHERYL ACETATE
CERAMIDE 3
CERAMIDE 6 II
CHOLESTEROL
MADECASSOSIDE

Package Label - Principal Display Panel

75728-004-01 15 g in 1 BOTTLE

75728-004-02 20 g in 1 BOTTLE

75728-004-03 30 g in 1 BOTTLE